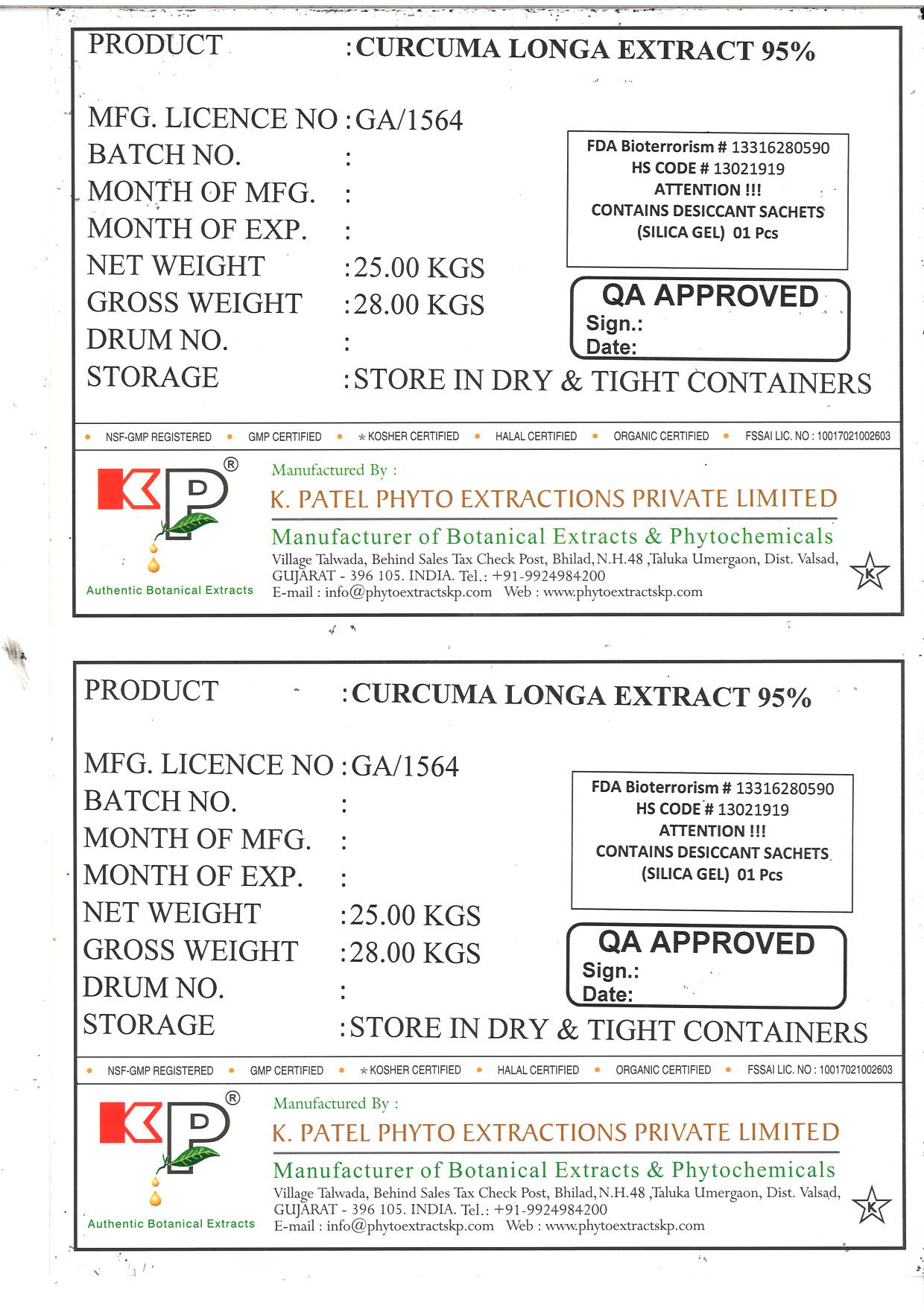 DRUG LABEL: Curcuma longa extract 95%
NDC: 73276-005 | Form: POWDER
Manufacturer: K. Patel Phyto Extractions Private Limited
Category: other | Type: BULK INGREDIENT
Date: 20250625

ACTIVE INGREDIENTS: CURCUMA LONGA (TURMERIC) ROOT 25 kg/25 kg

Curcuma longa extract 95%